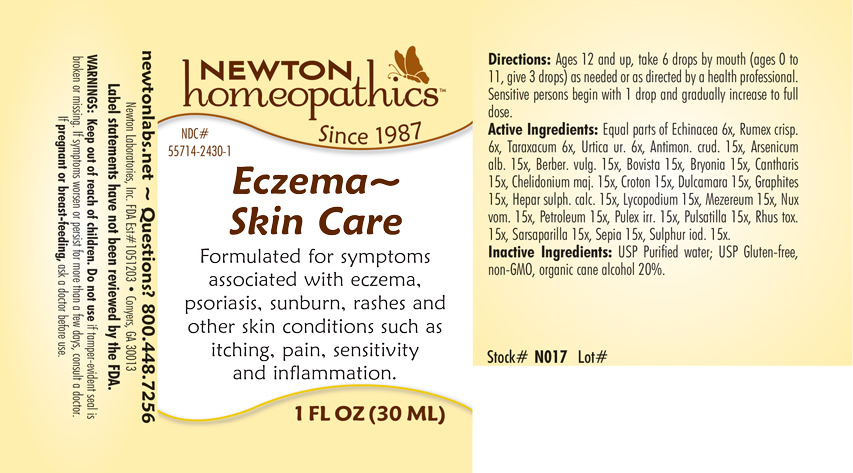 DRUG LABEL: Eczema - Skin Care
NDC: 55714-2430 | Form: LIQUID
Manufacturer: Newton Laboratories, Inc.
Category: homeopathic | Type: HUMAN OTC DRUG LABEL
Date: 20250206

ACTIVE INGREDIENTS: SARSAPARILLA 15 [hp_X]/1 mL; ANTIMONY TRISULFIDE 15 [hp_X]/1 mL; ARSENIC TRIOXIDE 15 [hp_X]/1 mL; BERBERIS VULGARIS ROOT BARK 15 [hp_X]/1 mL; GIANT PUFFBALL 15 [hp_X]/1 mL; BRYONIA ALBA ROOT 15 [hp_X]/1 mL; LYTTA VESICATORIA 15 [hp_X]/1 mL; CHELIDONIUM MAJUS 15 [hp_X]/1 mL; CROTON TIGLIUM SEED 15 [hp_X]/1 mL; SOLANUM DULCAMARA TOP 15 [hp_X]/1 mL; GRAPHITE 15 [hp_X]/1 mL; CALCIUM SULFIDE 15 [hp_X]/1 mL; LYCOPODIUM CLAVATUM SPORE 15 [hp_X]/1 mL; DAPHNE MEZEREUM BARK 15 [hp_X]/1 mL; STRYCHNOS NUX-VOMICA SEED 15 [hp_X]/1 mL; KEROSENE 15 [hp_X]/1 mL; PULEX IRRITANS 15 [hp_X]/1 mL; PULSATILLA VULGARIS 15 [hp_X]/1 mL; TOXICODENDRON PUBESCENS LEAF 15 [hp_X]/1 mL; SEPIA OFFICINALIS JUICE 15 [hp_X]/1 mL; SULFUR IODIDE 15 [hp_X]/1 mL; ECHINACEA, UNSPECIFIED 6 [hp_X]/1 mL; RUMEX CRISPUS ROOT 6 [hp_X]/1 mL; TARAXACUM OFFICINALE 6 [hp_X]/1 mL; URTICA URENS 6 [hp_X]/1 mL
INACTIVE INGREDIENTS: ALCOHOL; WATER

Eczema 2430L

INDICATIONS & USAGE SECTION

Formulated for symptoms associated with eczema, psoriasis, sunburn, rashes and other skin conditions such as itching, pain, sensitivity and inflammation.

DOSAGE & ADMINISTRATION SECTION

Directions: Ages 12 and up, take 6 drops by mouth (ages 0 to 11, give 3 drops) as needed or as directed by a health professional. Sensitive persons begin with 1 drop and gradually increase to full dose.

OTC - ACTIVE INGREDIENT SECTION

Equal parts of Echinacea 6x, Rumex crisp. 6x, Taraxacum 6x, Urtica ur, 6x, Antimon. crud. 15x, Arsenicum alb. 15x, Berber. vulg. 15x, Bovista 15x, Bryonia 15x, Cantharis 15x, Chelidonium majus 15x, Croton 15x, Dulcamara 15x, Graphites 15x, Hepar sulph. calc. 15x, Lycopodium 15x, Mezereum 15x, Nux vom. 15x, Petroleum 15x, Pulex irr. 15x, Pulsatilla 15x, Rhus tox. 15x, Sarsaparilla 15x, Sepia 15x, Sulphur iod. 15x.

OTC - PURPOSE SECTION

Formulated for symptoms associated with eczema, psoriasis, sunburn, rashes and other skin conditions such as itching, pain, sensitivity and inflammation.

INACTIVE INGREDIENT SECTION

Inactive Ingredients: USP Purified Water; USP Gluten-free, non-GMO, organic cane alcohol 20%.

QUESTIONS SECTION

newtonlabs.net - Questions? 800.448.7256

Newton Laboratories, Inc. FDA Est # 1051203 - Conyers, GA 30013

WARNINGS SECTION

WARNINGS: Keep out of reach of children. Do not use if tamper-evident seal is broken or missing. If symptoms worsen or persist for more than a few days, consult a doctor. If pregnant or breast-feeding, ask a doctor before use.

OTC - PREGNANCY OR BREAST FEEDING SECTION

If pregnant or breast-feeding, ask a doctor before use.

OTC - KEEP OUT OF REACH OF CHILDREN SECTION

Keep out of reach of children.